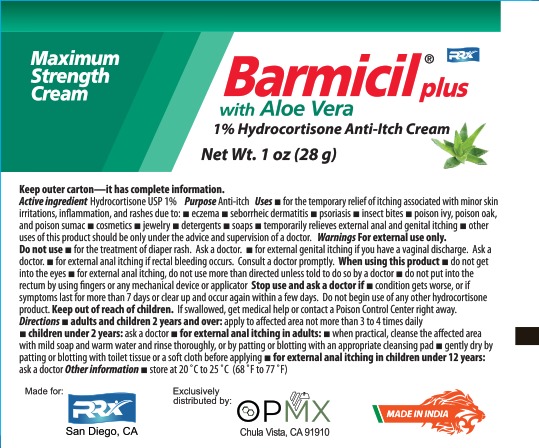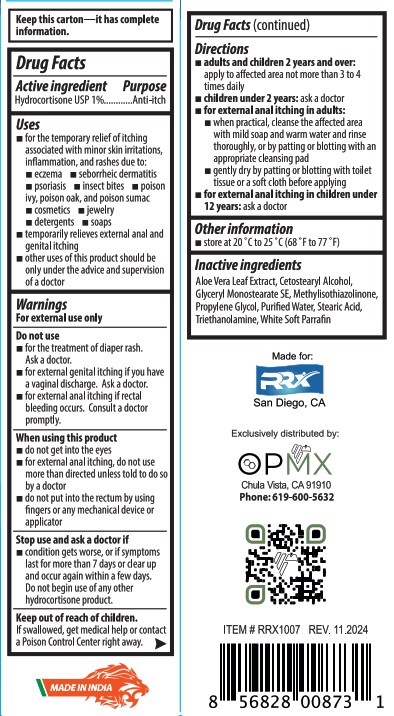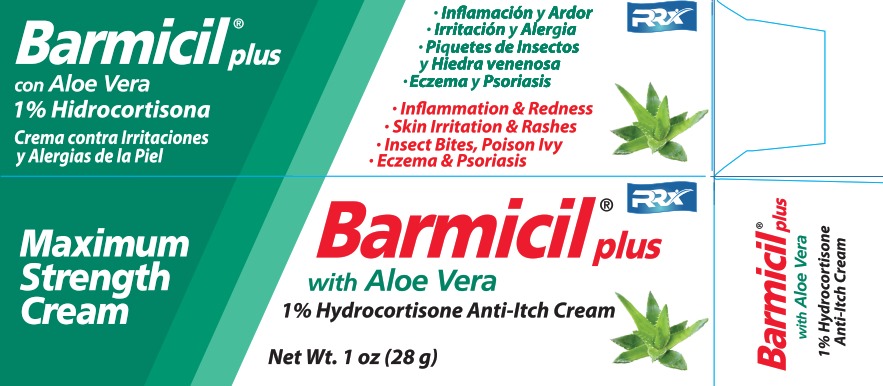 DRUG LABEL: BARMICIL PLUS
NDC: 69729-103 | Form: CREAM
Manufacturer: OPMX LLC
Category: otc | Type: HUMAN OTC DRUG LABEL
Date: 20241203

ACTIVE INGREDIENTS: HYDROCORTISONE 10 mg/1 g
INACTIVE INGREDIENTS: ALOE VERA LEAF; CETOSTEARYL ALCOHOL; GLYCERYL STEARATE SE; METHYLISOTHIAZOLINONE; PROPYLENE GLYCOL; WATER; STEARIC ACID; TROLAMINE; PARAFFIN

BARMICIL PLUS

ACTIVE INGREDIENTS

HYDROCORTISONE USP 1%

PURPOSE

ANTI-ITCH

USES

- FOR THE TEMPORARY RELIEF OF ITCHING ASSOCIATED WITH MINOR SKIN IRRITATIONS, INFLAMMATION, AND RASHES DUE TO:
- ECZEMA
- SEBORRHEIC DERMATITIS
- PSORIASIS
- INSECT BITES
- POISON IVY, POISON OAK, AND POISON SUMAC
- COSMETICS
- JEWELRY
- DETERGENTS
- SOAPS
- TEMPORARILY RELIEVES EXTERNAL ANAL AND GENITAL ITCHING
- OTHER USES OF THIS PRODUC SHOULD BE ONLY UNDER THE ADVICE AND SUPERVISION OF A DOCTOR

WARNINGS

For external use only.

DO NOT USE

- FOR THE TREATMENT OF DIAPER RASH. ASK A DOCTOR.
- FOR EXTERNAL GENITAL ITCHING IF YOU HAVE A VAGINAL DISCGARGE. ASK A DOCTOR.
- FOR EXTERNAL ANAL ITCHING IF RECTAL BLEEDING OCCURS. CONSULT A DOCTOR PROMPTLY.

WHEN USING THIS PRODUCT

- DO NOT GET INTO THE EYES
- FOR EXTERNAL ANAL ITCHING, DO NOT USE MORE THAN DIRECTED UNLESS TOLD TO DO SO BY A DOCTOR
- DO NOT PUT INTO THE RECTUM BY USING FINGERS OR ANY MECHANICAL DEVICE OR APPLICATOR

STOP USE AND ASK A DOCTOR IF

- CONDITION GETS WORSE, OR IF SYMPTOMS LAST FOR MORE THAN 7 DAYS OR CLEAR UP AND OCCUR AGAIN WITHIN A FEW DAYS. DO NOT BEGIN USE OF ANY OTHER HYDROQUINONE PRODUCT.

Keep out of reach of children. If swallowed get medical help or contact Poison Control Center right away.

DIRECTIONS

- ADULTS AND CHILDREN 2 YEARS AND OVER: APPLY TO AFFECTED AREA NOT MORE THAN 3 TO 4 TIMES DAILY.
- CHILDREN UNDER 2 YEARS: ASK A DOCTOR
- FOR EXTERNAL ANAL ITCHING IN ADULTS:
- WHEN PRACTICAL, CLEANSE THE AFFECTED AREA WITH MILD SOAP AND WARM WATER AND RINSE THOROUGHLY, OR BY PATTING OR BLOTTING WITH AN APPROPRIATE CLEANSING PAD
- GENTLY DRY BY PATTING OR BLOTTING WITH TOILET TISSUE OR A SOFT CLOTH BEFORE APPLYING.
- FOR EXTERNAL ANAL ITCHING IN CHILDREN UNDER 12 YEARS: ASK A DOCTOR.

OTHER INFORMATION

- STORE AT 20°C TO 25°C (68°F TO 77°F)

INACTIVE INGREDIENTS

ALOE VERA LEAF EXTRACT, CETOSTEARYL ALCOHOL, GLYCERYL MONOSTEARATE SE, METHYLISOTHIAZOLINONE, PROPYLENE GLYCOL, PURIFIED WATER, STEARIC ACID, TRIETHANOLAMINE, WHITE SOFT PARAFFIN

PACKAGE LABEL

Barmicil plus

with Aloe Vera

1% Hydrocortisone Anti-Itch Cream

Net Wt. 1 oz (28g)

Inflammation & Redness

Skin Irritation & Rashes

Insect Bites, Poison Ivy

Eczema & Psoriasis